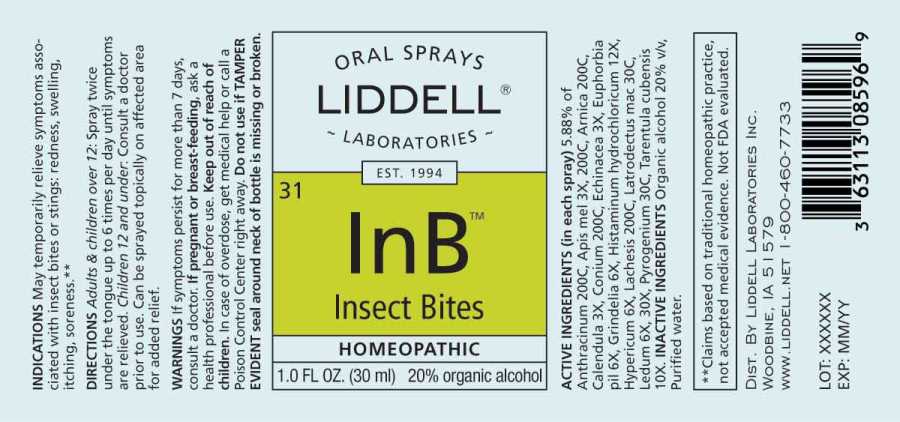 DRUG LABEL: Insect Bites
NDC: 50845-0277 | Form: LIQUID
Manufacturer: Liddell Laboratories, Inc.
Category: homeopathic | Type: HUMAN OTC DRUG LABEL
Date: 20240826

ACTIVE INGREDIENTS: BACILLUS ANTHRACIS IMMUNOSERUM RABBIT 200 [hp_C]/1 mL; APIS MELLIFERA 3 [hp_X]/1 mL; ARNICA MONTANA WHOLE 200 [hp_C]/1 mL; CALENDULA OFFICINALIS FLOWERING TOP 3 [hp_X]/1 mL; CONIUM MACULATUM FLOWERING TOP 200 [hp_C]/1 mL; ECHINACEA ANGUSTIFOLIA WHOLE 3 [hp_X]/1 mL; EUPHORBIA HIRTA FLOWERING TOP 6 [hp_X]/1 mL; GRINDELIA HIRSUTULA FLOWERING TOP 6 [hp_X]/1 mL; HISTAMINE DIHYDROCHLORIDE 12 [hp_X]/1 mL; HYPERICUM PERFORATUM WHOLE 6 [hp_X]/1 mL; LACHESIS MUTA VENOM 200 [hp_C]/1 mL; LATRODECTUS MACTANS 30 [hp_C]/1 mL; RHODODENDRON TOMENTOSUM LEAFY TWIG 6 [hp_X]/1 mL; RANCID BEEF 30 [hp_C]/1 mL; CITHARACANTHUS SPINICRUS 10 [hp_X]/1 mL
INACTIVE INGREDIENTS: WATER; ALCOHOL

DRUG FACTS:

ACTIVE INGREDIENTS:

(in each spray) 5.88% of Anthracinum 200C, Apis Mellifica 3X, 200C, Arnica Montana 200C, Calendula Officinalis 3X, Conium Maculatum 200C, Echinacea (Angustifolia) 3X, Euphorbia Pilulifera 6X, Grindelia 6X, Histaminum Hydrochloricum 12X, Hypericum Perforatum 6X, Lachesis Mutus 200C, Latrodectus Mactans 30C, Ledum Palustre 6X, 30X, Pyrogenium 30C, Tarentula Cubensis 10X.

INDICATIONS:

May temporarily relieve symptoms associated with insect bites or stings: redness, swelling, itching, soreness.**

**Claims based on traditional homeopathic practice, not accepted medical evidence. Not FDA evaluated.

WARNINGS:

If symptoms persist for more than 7 days, consult a doctor.

If pregnant or breast feeding, ask a health professional before use.

Keep out of reach of children. In case of overdose, get medical help or call a Poison Control Center right away.

Do not use if TAMPER EVIDENT seal around neck of bottle is missing or broken.

Keep out of reach of children. In case of overdose, get medical help or call Poison Control Center right away.

DIRECTIONS:

Adults & Children over 12: Spray twice under the tongue up to 6 times per day until symptoms are relieved.

Children 12 and under: Consult a doctor prior to use. Can be sprayed topically on affected area for added relief.

INDICATIONS:

May temporarily relieve symptoms associated with insect bites or stings: redness, swelling, itching, soreness.**

**Claims based on traditional homeopathic practice, not accepted medical evidence. Not FDA evaluated.

INACTIVE INGREDIENTS:

Organic alcohol 20% v/v, Purified water.

QUESTIONS:

DIST. BY LIDDELL LABORATORIES INC.

WOODBINE, IA 51579

WWW.LIDDELL.NET 1-800-460-7733

PACKAGE LABEL DISPLAY:

ORAL SPRAYS

LIDDELL

LABORATORIES

EST. 1994
31 InB

INSECT BITES

HOMEOPATHIC

1.0 FL. OZ (30 ml)